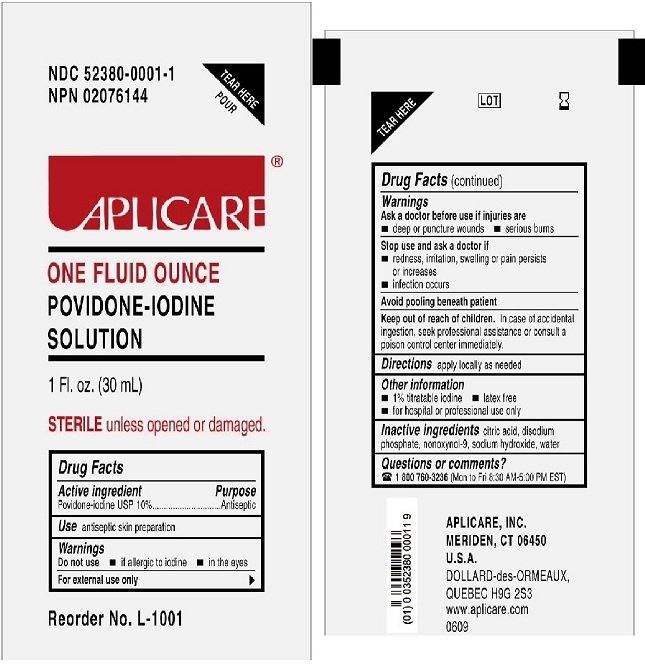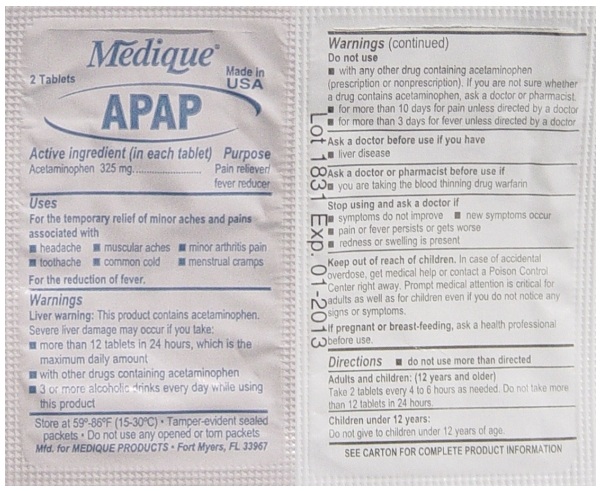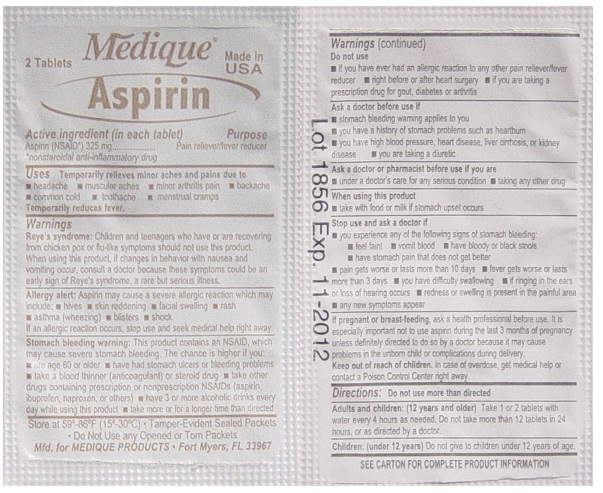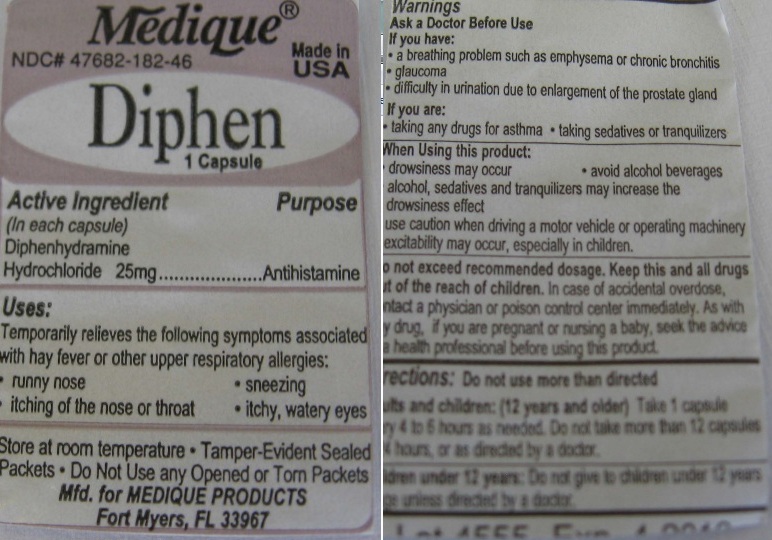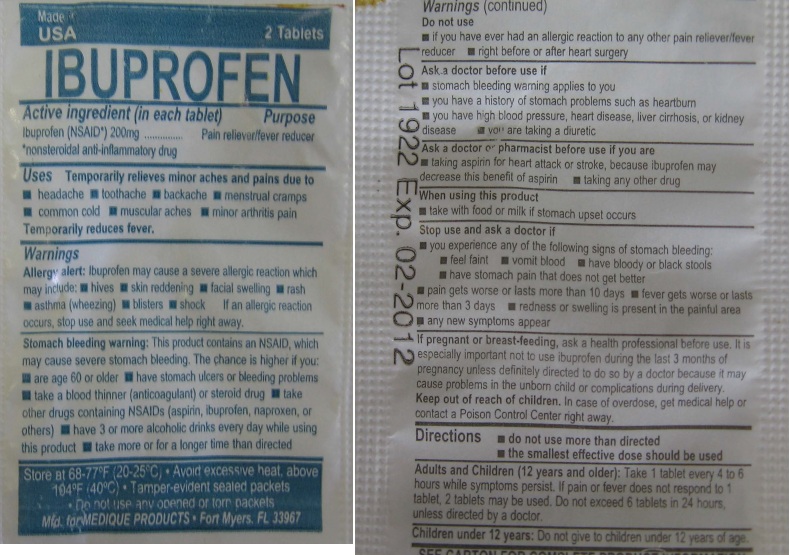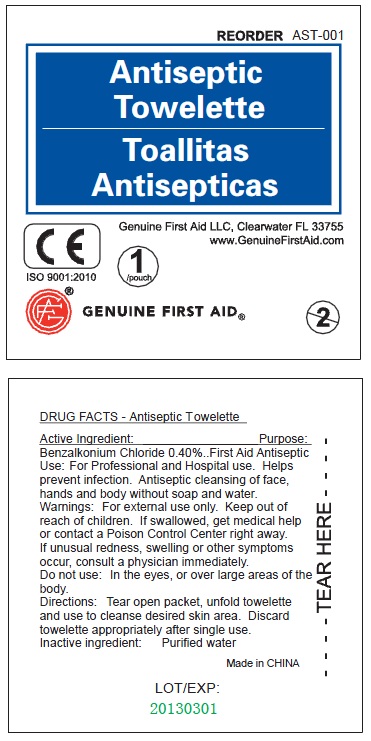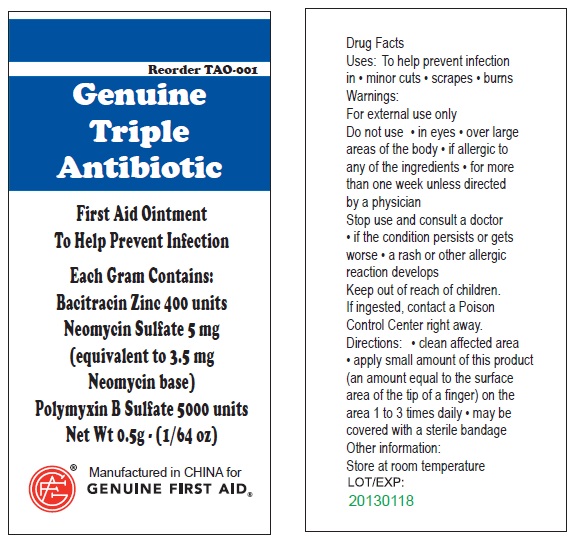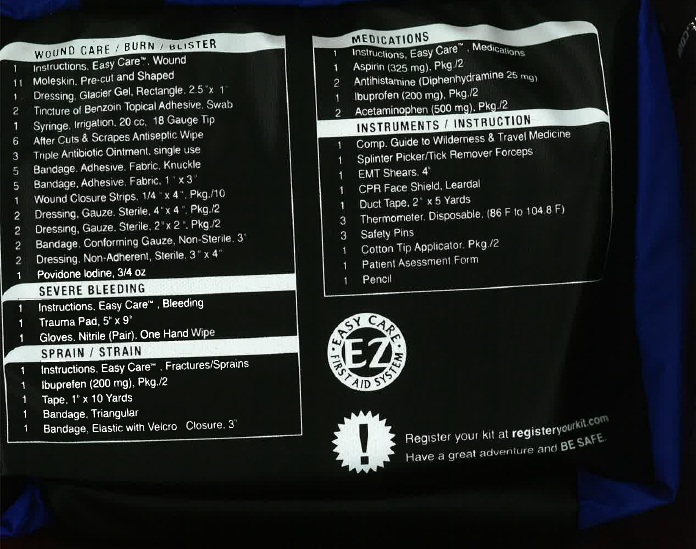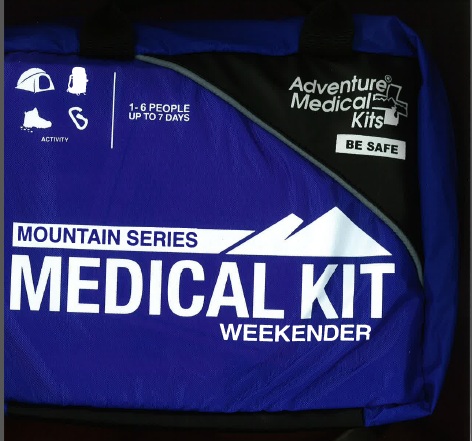 DRUG LABEL: Mountain Series Weekender Medical
NDC: 44224-0118 | Form: KIT | Route: TOPICAL
Manufacturer: Tender Corporation dba Adventure Medical Kits
Category: otc | Type: HUMAN OTC DRUG LABEL
Date: 20110801

ACTIVE INGREDIENTS: BENZALKONIUM CHLORIDE 0.40 mL/100 mL; BACITRACIN ZINC 400 [iU]/1 g; NEOMYCIN SULFATE 5 mg/1 g; POLYMYXIN B SULFATE 5000 [iU]/1 g; ASPIRIN 325 mg/1 1; DIPHENHYDRAMINE HYDROCHLORIDE 25 mg/1 1; IBUPROFEN 200 mg/1 1; ACETAMINOPHEN 325 mg/1 1; POVIDONE-IODINE 9.8 g/100 g
INACTIVE INGREDIENTS: WATER; WATER; HYPROMELLOSES; POLYETHYLENE GLYCOL; PROPYLENE GLYCOL; STARCH, CORN; D&C RED NO. 28; FD&C BLUE NO. 1; FD&C RED NO. 40; GELATIN; STARCH, CORN; CELLULOSE, MICROCRYSTALLINE; HYPROMELLOSES; LACTOSE; MAGNESIUM STEARATE; POLYDEXTROSE; POLYETHYLENE GLYCOL; POVIDONE; SILICON DIOXIDE; STARCH, CORN; STEARIC ACID; TITANIUM DIOXIDE; TRIACETIN; HYPROMELLOSES; POLYETHYLENE GLYCOL; POVIDONE; SODIUM STARCH GLYCOLATE TYPE A POTATO; STARCH, CORN; STEARIC ACID; CITRIC ACID MONOHYDRATE; SODIUM PHOSPHATE, DIBASIC; SODIUM HYDROXIDE; NONOXYNOL-9; WATER

Mountain Series Weekender Medical Kit

Active Ingredient

Benzalkonium Chloride 0.40%

Purpose

Antiseptic

Use

For Professional and Hospital use. Helps prevent infection. Antiseptic cleansing of face, hands and body without soap and water.

Warnings

Warning: For external use only.

Keep out of reach of children: If swallowed, get medical help or contact a Poison Control Center right away.

Stop use if unusual redness, swelling or other symptoms occur. Consult a physician immediately.

Do not use in the eyes or over large areas of the body.

Directions

Tear open packet, unfold towelette and use to cleanse desired skin area. Discard towelette appropriately after single use.

Inactive Ingredients

Inactive Ingredient: Purified water

LOT/EXP: Made in CHINA

20130301

PACKAGE LABEL

Antiseptic Towelette

Genuine First Aid LLC, Clearwater FL 33755

www.GenuineFirstAid.com

1/pouch

GENUINE FIRST AID

Active Ingredients

Active Ingredient: .........Bacitracin Zinc 400 units

Neomycin Sulfate 5mg (equivalent to 3.5 mg Neomycin base)

Polymyxin B Sulfate 5000 units

Purpose

Triple Antibiotic

INDICATIONS AND USAGE

Uses: To help prevent infection in:
minor cuts; scrapes; burns

Warnings

For external use only.

Do not use: in eyes; over large areas of the body;

If allergic to any of the ingredients; for more than one week unless directed by a physician.

Stop use and consult a doctor:

if the condition persists or gets worse; a rash or other allergic reaction develops

Keep out of reach of children.

If ingested, contact a Poison

Control Center right away.

Directions

Directions: clean affected area; apply small amount of this product (an amount equal to the surface area of the tip of a finger) on the area 1 to 3 times daily; may be covered with a sterile bandage

Other information:

Store at room temperature.

Inactive Ingredient

water

PACKAGE LABEL

Genuine Triple Antibiotic

First Aid Ointment

To Help Prevent Infection

Each Gram Contains:

Bacitracin Zinc 400 units

Neomycin Sulfate 5 mg

(equivalent to 3.5 mg

Neomycin base)

Polymyxin B Sulfate 5000 units

Net Wt. 0.5g ; (1/64 oz)

Manufactured in CHINA for

GENUINE FIRST AID.

Triple Antibiotic Ointment 10pcs

Net wt. 0.9g (1/32oz)

100
Triple Antibiotic

Active ingredient (in each tablet)

Aspirin (NSAID*) 325 mg

*nonsteroidal anti-inflammatory drug

Purpose

Pain reliever/fever reducer

Uses

Temporarily relieves minor aches and pains associated with

- headache
- minor arthritis
- common cold
- menstrual cramps
- muscular aches
- backache
- toothache

Temporarily reduces fever.

Warnings

Reye's syndrome: Children and teenagers who have or are recovering from chicken pox or flu-like symptoms should not use this product. When using this product, if changes in behavior with nausea and vomiting occur, consult a doctor because these symptoms could be an early sign of Reye's syndrome, a rare but serious illness.

Stomach bleeding warning: This product contains an NSAID, which may cause severe stomach bleeding. The chance is higher if you:

- are age 60 or older
- have had stomach ulcers or bleeding problems
- take a blood thinning (anticoagulant) or steroid drug
- take other drugs containing prescription or nonprescription
  NSAIDs (aspirin, ibuprofen, naproxen, or others)
- have 3 or more alcohol drinks every day while
  using this product
- take more or for a longer time than directed

Do not use

- if you have ever had an allergic reaction to any other pain reliever/ fever reducer
- right before or after heart surgery
- if you are taking prescription drugs for gout, diabetes or arthritis

Ask a doctor before use if

- stomach bleeding warning applies to you
- you have a history of stomach problems such as heartburn
- you have high blood pressure, heart disease, liver cirrhosis, or kidney disease
- you are taking a diuretic

Ask a doctor or pharmacist before use if you are

- under a doctor's care for any serious condition
- taking any other drug

When using this product

- take with food or milk if stomach upset occurs

Stop use and ask a doctor if

- you experience any of the following signs of stomach bleeding:
- feel faint
- vomit blood
- have bloody or black stools
- have stomach pain that does not get better
- pain gets worse or lasts more than 10 days
- fever gets worse or lasts more than 3 days
- you have difficulty swallowing
- if ringing in the ears or loss of hearing occurs redness or swelling is present in the painful area
- any new symptoms appear

PREGNANCY OR BREAST FEEDING

If pregnant or breast-feeding, ask a health professional before use. It is especially important not to use aspirin during the last 3 months of pregnancy unless definitely directed to do so by a doctor because it may cause problems in the unborn child or complications during delivery.

Keep out of reach of children. In case of overdose, get medical help or contact a Poison Control Center right away.

Directions

- do not take more than directed
- the smallest effective dose should be used
- do not take longer than 10 days, unless
  directed by a doctor (see Warnings)
- drink a full glass of water with each dose

Adults and children: (12 years and older)

Take 1 or 2 tablets with water every 4 hours as needed. Do not take more than 12 tablets in 24 hours, or as directed by a doctor.

Children under 12 years:

Do not give to children under 12 years of age.

Other information

- read all product information before using
- store at room temperature 59º-86ºF (15º-30ºC)
- avoid excessive heat and humidity
- tamper evident sealed packets
- do not use any opened or torn packets

Inactive ingredients

croscarmellose sodium*, hypromellose, microcrystalline cellulose*, mineral oil*, polyethylene glycol*, propylene glycol*, starch, titanium dioxide*

*may contain

Questions or comments?

1-800-634-7680

116R Medique APAP 325 mg Label

Medique®

Aspirin

5 Grain (325 mg)

Pain Reliever/Fever Reducer (NSAID)

See new warnings information

East To Swallow

Film Coated Tablets

24 Tablets

(12 x 2)

Compare active ingredients to Bayer®

Registered Trademark Bayer Consumer

Tamper Evident Unit Dose Packets

Active ingredients

(in each capsule)

Diphenhydramine Hydrochloride 25 mg

Purpose

Antihistamine

Uses

Temporarily relieves runny nose and decreases sneezing, itching of the nose and throat, itchy-watery eyes due to hay fever or other respiratory allergies.

Warnings

Do not use

- with any other product containing diphenhydramine, even one that is used on skin.

Ask a doctor before use if you have

- a breathing problem such as emphysema or chronic bronchitis
- difficulty in urination due to enlargement of the prostate gland
- glaucoma

Ask a doctor or pharmacist before use if you are

- taking any drugs for asthma
- taking sedatives or tranquilizers

When Using This Product

- marked drowsiness may occur
- avoid alcohol beverages
- alcohol, sedatives and tranquilizers may increase the drowsiness effect
- use caution when driving a motor vehicle or operating machinery
- excitability may occur, especially in children

PREGNANCY OR BREAST FEEDING

If pregnant or breast feeding, ask a health professional before use.

KEEP OUT OF REACH OF CHILDREN

Keep out of the reach of children. In case of overdose, contact a physician or poison control center immediately.

Directions

- do not use more than directed

Adults and children: (12 years and older): Take 1 to 2 capsules every 4 to 6 hours as needed. Do not take more than 12 capsules in 24 hours.

Children under 12 years: Do not give to children under 12 years of age.

Other information

- store at room temperature 59º-86ºF (15º-30ºC)
- tamper-evident sealed packets
- do not use any opened or torn packets

Inactive ingredients

D&C Red #28, FD&C Blue #1, FD&C Red #40, gelatin, starch

182R Medique Diphen Label

Collect Medi-Bucks

See inside flap for more details

Medique®

Diphen

Diphenhydramine HCl 25 mg

Hay Fever/Allergies

Fiebre del Heno/Alergias

Pull to Open

TiraParaAbrir

Easy To Swallow Capsules

Capsulas Faciles de Tragar

200 Capsules

(200 x 1)

Tamper Evident Unit Dose Packets

Empaquetado con Sellado Evidente en Dosis Untarias

Active ingredient
(in each tablet)

Ibuprofen (NSAID*) 200 mg

*nonsteroidal anti-inflammatory drug

Purpose

Pain reliever/fever reducer

Uses

Temporarily relieves minor aches and pains associated with

■ headache
■ backache
■ common cold
■ minor arthritis pain
■ toothache
■ menstrual cramps
■ muscular aches

Temporarily reduces fever.

Warnings

Allergy alert: Ibuprofen may cause a severe allergic reaction which may include:

- hives
- asthma (wheezing)
- rash
- blisters
- skin reddening
- facial swelling
- shock

If an allergic reaction occurs, stop use and seek medical help right away.

Stomach bleeding warning: This product contains an NSAID, which may cause severe stomach bleeding. The chance is higher if you:

- are age 60 or older
- have had stomach ulcers or bleeding problems
- take a blood thinning (anticoagulant) or steroid drug
- take other drugs containing prescription or nonprescription NSAIDs (aspirin, ibuprofen, naproxen, or others)
- have 3 or more alcoholic drinks every day while using this product
- take more or for a longer time than directed

Do not use

- if you have ever had an allergic reaction to any other pain reliever/fever reducer
- right before or after heart surgery

Ask a doctor before use if

- stomach bleeding warning applies to you
- you have a history of stomach problems such as heartburn
- you have high blood pressure, heart disease, liver cirrhosis, or kidney disease
- you are taking a diuretic

Ask a doctor or pharmacist before use if you are

- taking aspirin for heart attack or stroke, because ibuprofen may decrease this benefit of aspirin
- taking any other drug

When using this product

- take with food or milk if stomach upset occurs

Stop use and ask a doctor if

- you experience any of the following signs of stomach bleeding:
  - feel faint
  - vomit blood
  - have bloody or black stools
  - have stomach pain that does not get better
  - pain gets worse or lasts for more than 10 days
  - fever gets worse or lasts for more than 3 days
  - redness or swelling is present in the painful area
- any new or unexpected symptoms occur

PREGNANCY OR BREAST FEEDING

If pregnant or breast-feeding, ask a health professional before use. It is especially important not to use ibuprofen during the last 3 months of pregnancy unless specifically directed to so by a doctor because it may cause problems in the unborn child or complications during delivery.

Keep out of reach of children. In case of overdose, get medical help or contact a Poison Control Center right away.

Directions

- do not use more than directed
- the smallest effective dose should be used
- do not take longer than 10 days, unless directed by a doctor (see Warnings)

Adults and children: (12 years and older)

Take 1 tablet every 4 to 6 hours while symptoms persist. If pain or fever does not respond to 1 tablet, 2 tablets may be used. Do not exceed 6 tablets in 24 hours, unless directed by a doctor.

Children under 12 years:

Do not give to children under 12 years of age.

Other information

- read all product information before using
- store at 68-77°F (20-25°C)
- avoid excessive heat 40°C (above 104°F)
- tamper evident sealed packets
- do not use any opened or torn packets

Inactive ingredients

carnauba wax*, cellulose*, colloidal silicon dioxide, corn starch*, hypromellose, iron oxide red*, lactose, magnesium stearate, microcrystalline cellulose*, polydextrose, polyethylene glycol, povidone, silica*, sodium lauryl sulfate*, sodium starch glycolate, stearic acid*, titanium dioxide, triacetin*

*may contain

Questions or comments? 1-800-634-7680

Principal Display Panel

Medi-First®
Ibuprofen 200 mg
Pain Reliever/Fever Reducer (NSAID)
Easy To Swallow Film Coated Tablets
See new warnings information
100 tablets (50 x 2)
Compare active ingredient to: Genuine Advil®
Registered trademark Wyeth Consumer
Tamper Evident Unit Dose Packets

Active ingredient (in each tablet)

Acetaminophen 325 mg

Purpose

Pain reliever/fever reducer

Uses

For the temporary relief of minor aches and pains associated with

- headache
- common cold
- muscular aches
- toothache
- minor arthritis pain
- menstrual cramps

For the reduction of fever.

Warnings

Liver warning: This product contains acetaminophen. Severe liver damage may occur if you take:

- more than 12 tablets in 24 hours, which is the maximum daily amount
- with other drugs containing acetaminophen
- 3 or more alcoholic drinks every day while using this product

Do not use

- with any other drug containing acetaminophen (prescription or nonprescription). If you are not sure whether a drug contains acetaminophen, ask a doctor or pharmacist.
- for more than 10 days for pain unless directed by a doctor
- for more than 3 days for fever unless directed by a doctor

Ask a doctor before use if you have

- liver disease

Ask a doctor or pharmacist before use if

- you are taking the blood thinning drug warfarin

Stop using and ask a doctor if

- symptoms do not improve
- new symptoms occur
- pain or fever persists or gets worse
- redness or swelling is present

Keep out of reach of children. In case of accidental overdose, get medical help or contact a Poison Control Center right away. Prompt medical attention is critical for adults as well as for children even if you do not notice any signs or symptoms.

PREGNANCY OR BREAST FEEDING

If pregnant or breast-feeding, ask a health professional before use.

Directions

- do not use more than directed

Adults and children: (12 years and older)

Take 2 tablets every 4 to 6 hours as needed. Do not take more than 12 tablets in 24 hours.

Children under 12 years:

Do not give to children under 12 years of age.

Other information

- store at room temperature 59°-86°F (15°-30°C)
- tamper-evident sealed packets
- do not use any opened or torn packets

Inactive ingredients

corn starch, hypromellose, maltodextrin*, microcrystalline cellulose*, polyethylene glycol, povidone, pregelatinized starch*, sodium starch glycolate, stearic acid

* may contain

145R Medique APAP 325 mg Label

Collect MediBucks

See inside flap for more details

Medique®

APAP

Acetaminophen 325 mg

Pain Reliever/Fever Reducer

Alivia el Dolor/Reduce la Fiebre

Easy To Swallow

Film Coated Tablets

Facil de Tragar Tabletas con Cubierta Pelicular

Pull to Open

Tire Para Abrir

See new warnings information

500 Tablets

(250 x 2)

Tamper Evident Unit Dose Packets

Empaquetado con Sellado Evidente en Dosis Unitarias

Weekender Kit Label

Mountain Series Medical Kit Weekender

Adventure Medical Kits BE SAFE

1-6 People up to 7 days

ACTIVE INGREDIENT

Povidone-iodine 10%

PURPOSE

Antiseptic

Warnings

Do not use

- if allergic to iodine
- in the eyes

For external use only

Ask a doctor before use if injuries are

- deep or puncture wounds
- serious burns

Stop use and ask a doctor if

- redness, irritation, swelling or pain persists or increases
- infection occurs

Avoid pooling beneath patient

Keep out of reach of children. In case of accidental ingestion, seek professionalassistance or consult a poison control center immediately.